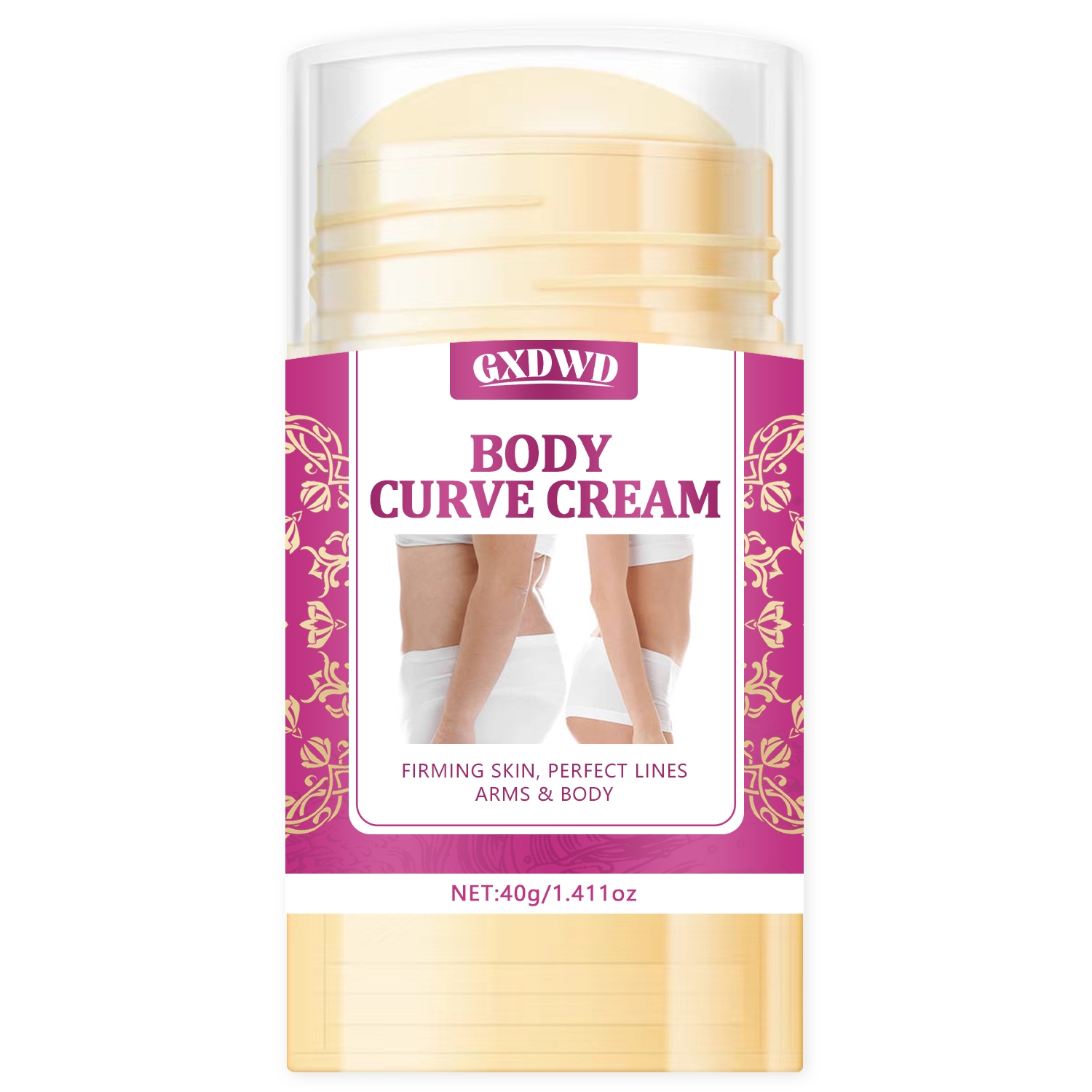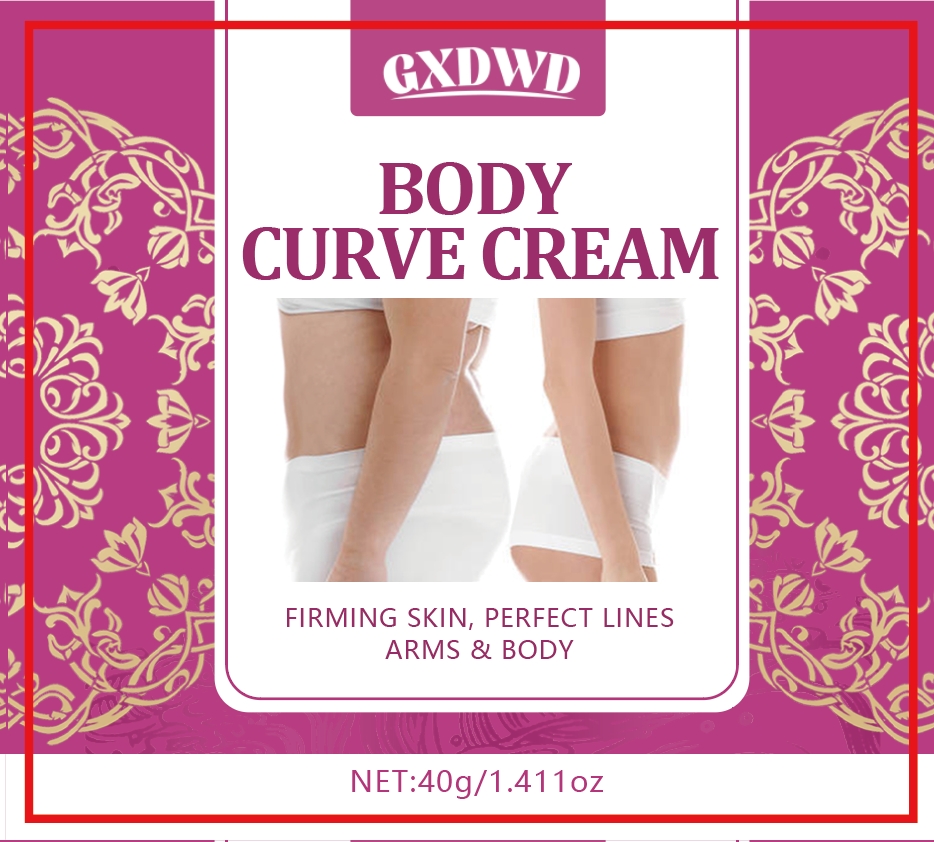 DRUG LABEL: BODY CURVECREAM
NDC: 84025-132 | Form: CREAM
Manufacturer: Guangzhou Yanxi Biotechnology Co.. Ltd
Category: otc | Type: HUMAN OTC DRUG LABEL
Date: 20240813

ACTIVE INGREDIENTS: NIACINAMIDE 5 mg/40 g; CETEARYL OLIVATE 3 mg/40 g
INACTIVE INGREDIENTS: WATER

DOSAGE AND ADMINISTRATION

Cream for moisturizing and caring for the skin

WARNINGS

Keep out of children

INACTIVE INGREDIENT

Aqua

INDICATIONS AND USAGE

For daily skin care

Keep out of children

PURPOSE

Firms skin and beautifies body lines